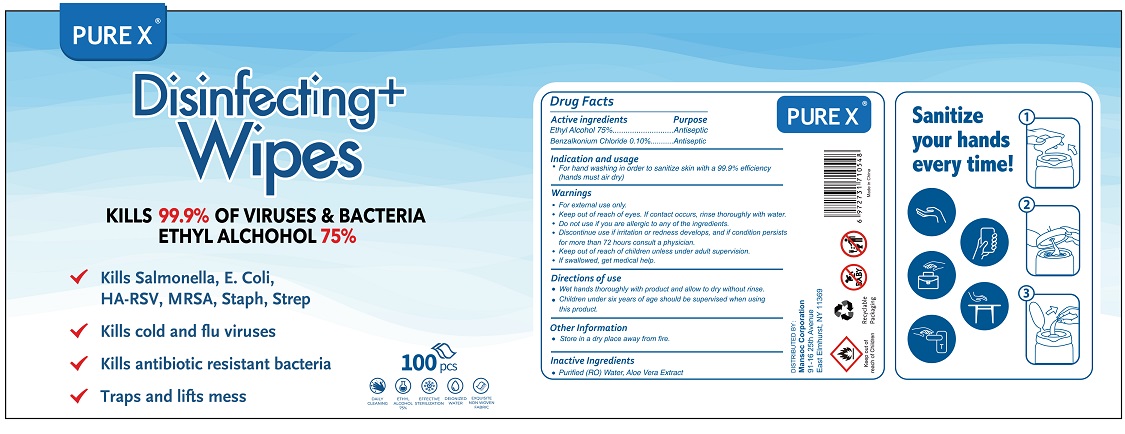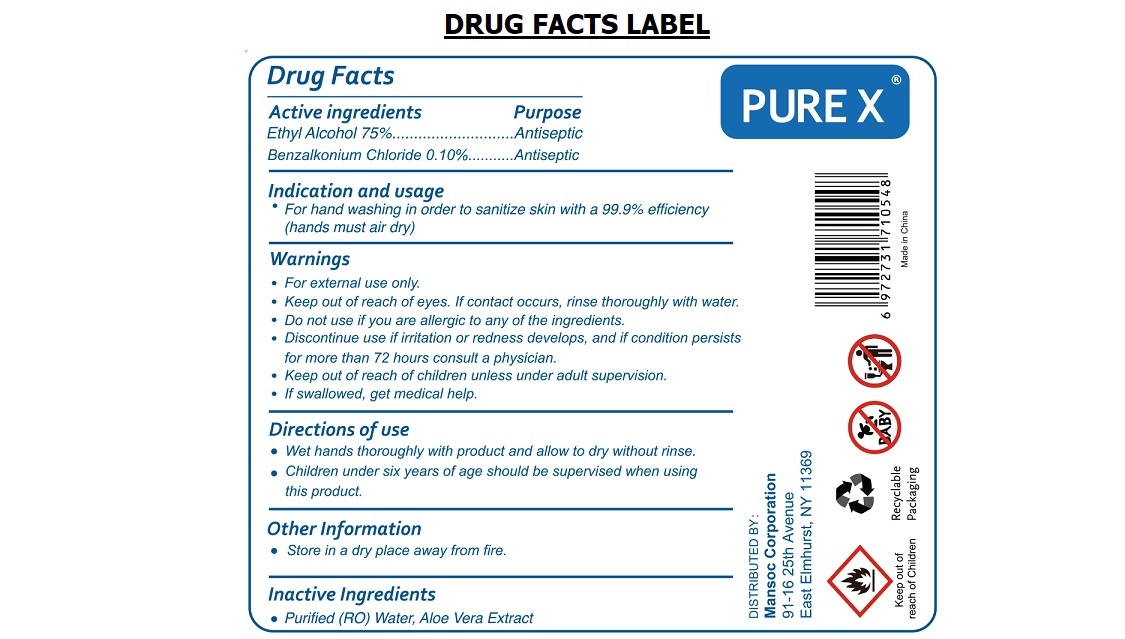 DRUG LABEL: Pure X Disinfecting Wipes
NDC: 80443-075 | Form: CLOTH
Manufacturer: Snapsak Ltd
Category: otc | Type: HUMAN OTC DRUG LABEL
Date: 20201111

ACTIVE INGREDIENTS: ALCOHOL 75 mL/100 mL; BENZALKONIUM CHLORIDE 0.1 g/100 mL
INACTIVE INGREDIENTS: WATER; ALOE VERA LEAF

PURE X® Disinfecting^+ Wipes

Active ingredients

Ethyl Alcohol 75%

Benzalkonium Chloride 0.10%

Purpose

Antiseptic

Indication and usage

• For hand washing in order to sanitize skin with a 99.9% efficiency (hands must air dry)

Warnings

• For external use only.

• Keep out of reach of eyes. If contact occurs, rinse thoroughly with water.

• Do not use if you are allergic to any of the ingredients.

• Discontinue use if irritation or redness develops, and if condition persists for more than 72 hours consult a physician.

• Keep out of reach of children unless under adult supervision.

• If swallowed, get medical help

Directions of use

• Wet hands thoroughly with product and allow to dry without rinse.

• Children under six years of age should be supervised when using this product.

Other Information

• Store in a dry place away from fire.

Inactive Ingredients

• Purified (RO) Water, Aloe Vera Extract

KILLS 99.9% OF VIRUSES & BACTERIA

√ Kills Salmonella, E. Coli, HA-RSV, MRSA, Staph, Strep

√ Kills cold and flu viruses

√ Kills antibiotic resistant bacteria

√ Traps and lifts mess

DAILY CLEANING

EFFECTIVE STERILIZATION

DEIONIZED WATER

EXQUISITE NON WOVEN FABRIC

DISTRIBUTED BY:

Mansoc Corporation

91-16 25th Avenue

East Elmhurst, NY 11369

Made in China

Sanitize your hands every time!